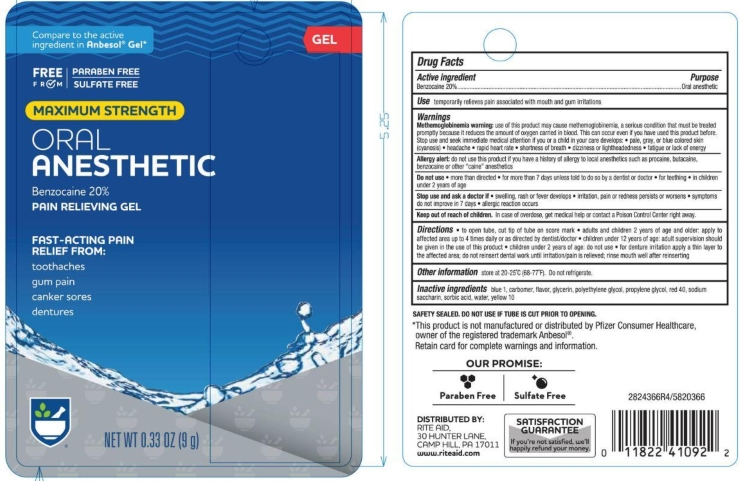 DRUG LABEL: Rite Aid
NDC: 11822-0316 | Form: GEL, DENTIFRICE
Manufacturer: Rite Aid
Category: otc | Type: HUMAN OTC DRUG LABEL
Date: 20251121

ACTIVE INGREDIENTS: BENZOCAINE 20 g/100 g
INACTIVE INGREDIENTS: POLYETHYLENE GLYCOL 400; PROPYLENE GLYCOL; SACCHARIN SODIUM; SORBIC ACID; GLYCERIN; FD&C RED NO. 40; D&C YELLOW NO. 10; FD&C BLUE NO. 1; WATER; CARBOMER HOMOPOLYMER TYPE B (ALLYL PENTAERYTHRITOL OR ALLYL SUCROSE CROSSLINKED)

5820366 Rite Aid Max Str Oral Pain Relief Gel

Drug Facts

Active ingredient

Benzocaine 20%

Purpose

Oral anesthetic

Use

temporarily relieves pain associated with mouth and gum irritations

Warnings

Methemoglobinemia warning: use of this product may cause methemoglobinemia, a serious condition that must be treated promptly because it reduces the amount of oxygen carried in blood. This can occur even if you have used this product before. Stop use and seek immediate medical attention of you or a child in your care develops:

- pale, gray, or blue colored skin (cyanosis)
- headache
- rapid heart rate
- shortness of breath
- dizziness or lightheadedness
- fatigue or lack of energy

Allergy alert: do not use this product if you have a history of allergy to local anesthetics such as procaine, butacaine, benzocaine or other “caine” anesthetics

Do not use

- more than directed
- for more than 7 days unless told to do so by a dentist or doctor
- for teething
- in children under 2 years of age

Stop use and ask a doctor if

- swelling, rash or fever develops
- irritation, pain or redness persists or worsens
- symptoms do not improve in 7 days
- allergic reaction occurs

Keep out of reach of children. In case of overdose, get medical help or contact a Poison Control Center right away.

Directions

- to open tube, cut tip of tube on score mark
- adults and children 2 years of age and older: apply to affected area up to 4 times daily or as directed by dentist/doctor
- children under 12 years of age: adult supervision should be given in the use of this product
- children under 2 years of age: do not use
- for denture irritation apply a thin layer to the affected area; do not reinsert dental work until irritation/pain is relieved; rinse mouth well after reinserting

Other information

store at 20-25°C (68-77°F). Do not refrigerate.

INACTIVE INGREDIENT

Inactive ingredients Blue 1, Carbomer, Flavor, Glycerin, Polyethylene Glycol, Propylene Glycol, Red 40, Sodium Saccharin, Sorbic Acid, Water, Yellow 10

DISTRIBUTED BY:

RITE AID, 30 HUNTER LANE

CAMP HILL, PA 17011